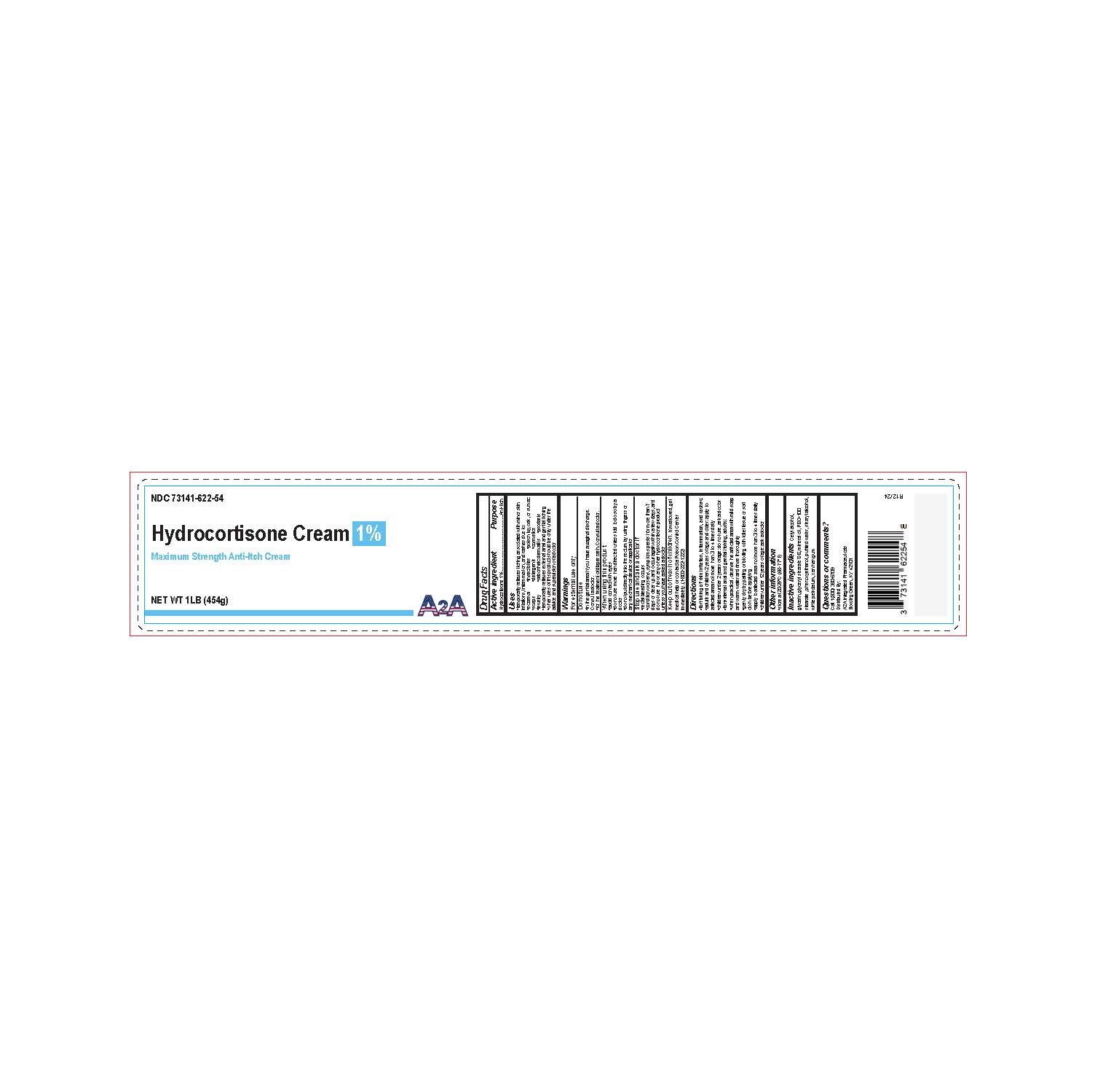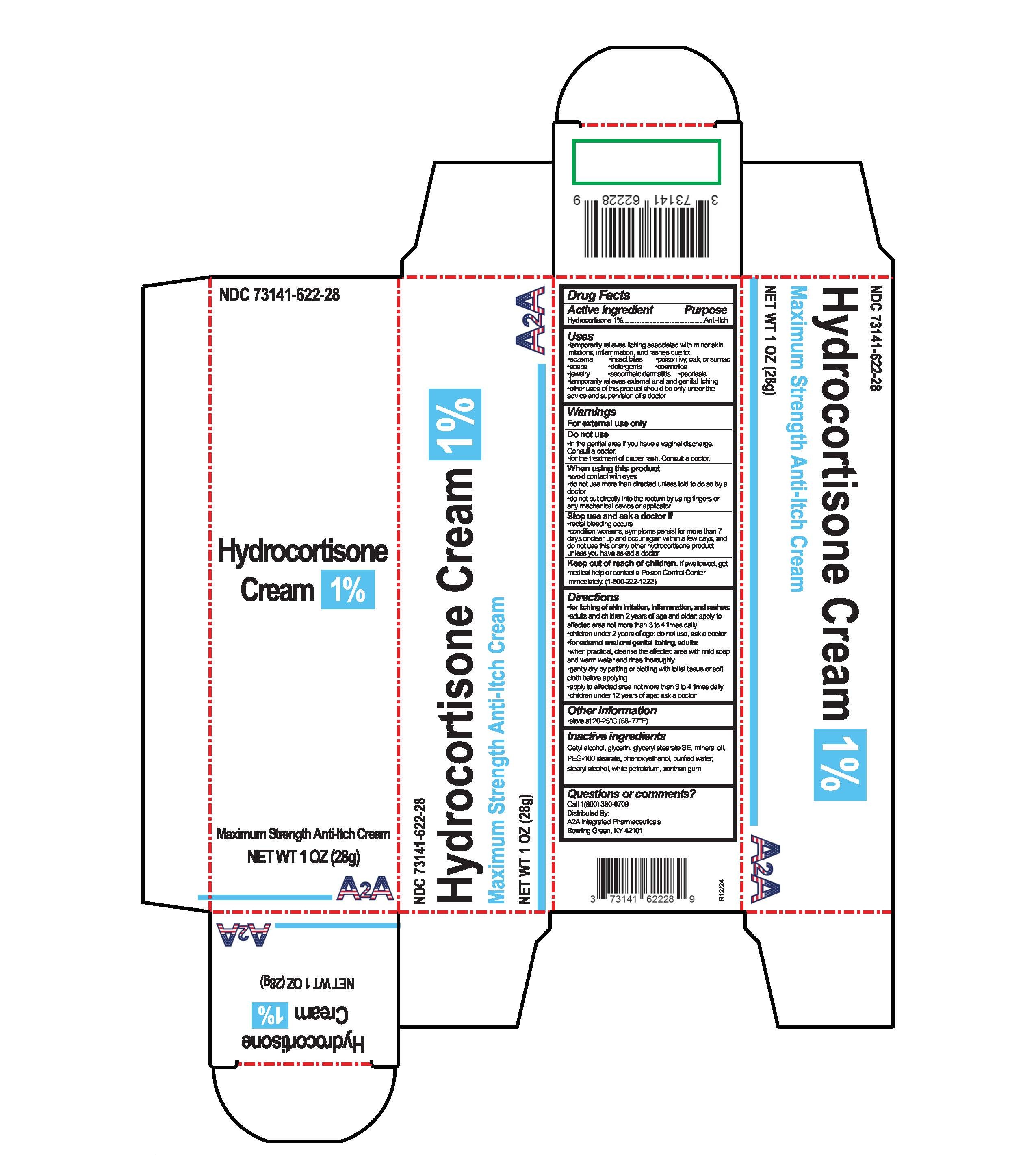 DRUG LABEL: Hydrocortisone
NDC: 73141-622 | Form: CREAM
Manufacturer: A2A Integrated Pharmaceuticals, LLC
Category: otc | Type: HUMAN OTC DRUG LABEL
Date: 20250331

ACTIVE INGREDIENTS: HYDROCORTISONE 10 mg/1 g
INACTIVE INGREDIENTS: WATER; GLYCERIN; PHENOXYETHANOL; PEG-100 STEARATE; MINERAL OIL; CETYL ALCOHOL; WHITE PETROLATUM; STEARYL ALCOHOL; GLYCERYL STEARATE SE; XANTHAN GUM

HYDROCORTISONE 1% CREAM

Active ingredient

Hydrocortisone 1%

Purpose

Anti-Itch

Uses

- temporarily relieves itching associated with minor skin irritations, inflammation, and rashes due to:
- eczema
- insect bites
- poison ivy, oak, or sumac
- soaps
- detergents
- cosmetics
- jewelry
- seborrheic dermatitis
- psoriarsis
- temporarity relieves external anal and genital itching
- other uses of this product should be only under the advice and supervision of a doctor

Warnings

For external use only

Do not use

- in the genital area if you have a vaginal discharge. Consult a doctor.
- for the treatment of diaper rash. Consult a doctor.

When using this product

- avoid contact with eyes
- do not use more than directed unless told to do so by a doctor
- do not put directly into the rectum by using fingers or any mechanical device or applicator

Stop use and ask a doctor if

- rectal bleeding occurs
- condition worsens, symptoms persist for more than 7 days or clear up and occur again within a few days, and do not use this or any other hydrocortisone product unless you have asked a doctor

Keep out of reach of children.

If swallowed, get medical help or contact a Poison Control Center immediately. (1-800-222-1222)

Directions

- for itching of skin irritation, inflammation, and rashes:
- adults and children 2 years of age and older: apply to affected area not more than 3 to 4 times daily
- children under 2 years of age: do not use, ask a doctor
- for external anal and genital itching, adults:
- when practical, cleanse the affected area with mild soap and warm water and rinse thoroughly
- gently dry by patting or blotting with toilet tissue or soft cloth before applying
- apply to affected area not more than 3 to 4 times daily
- children under 12 years of age: ask a doctor

Other information

- store at 20-25°C (68-77°F)

Inactive ingredients

Cetyl alcohol, glycerin, glyceryl stearate SE, mineral oil, PEG-100 stearate, phenoxyethanol, purified water, stearyl alcohol, white petrolatum, xanthan gum

Questions or comments?

Call 1(800)380-6709

Distributed By:

A2A Integrated Pharmaceuticals

Bowling Green, KY 42101

Carton Label

NDC 73141-622-28

Hydrocortisone Cream 1%

Maximum Strength Anti-Itch Cream

NET WT 1 OZ (28g)

Jar Label

NDC 73141-622-54

Hydrocortisone Cream 1%

Maximum Strength Anti-Itch Cream

NET WT 1LB (454g)